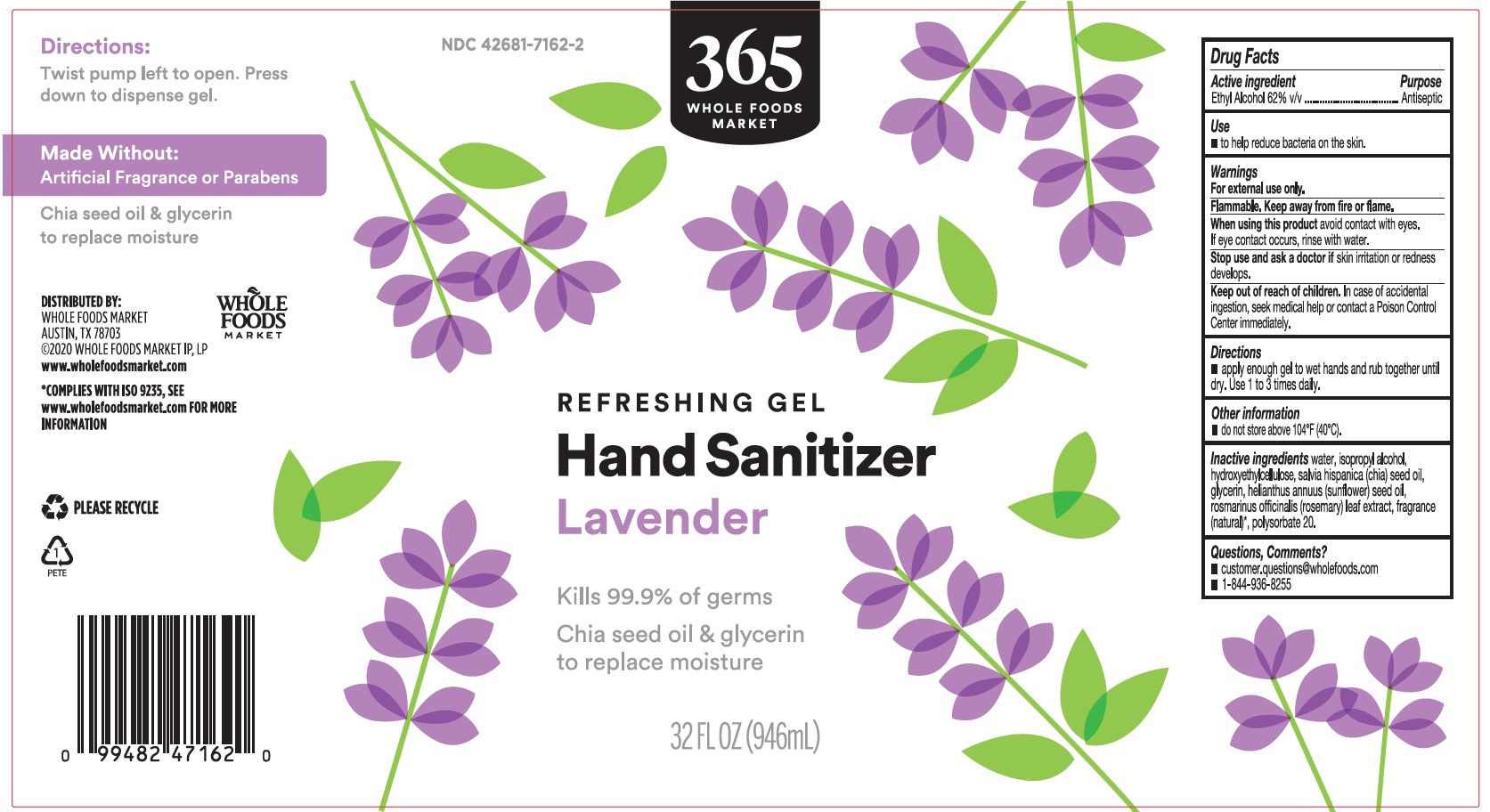 DRUG LABEL: Hand Sanitizer
NDC: 42681-7162 | Form: GEL
Manufacturer: Whole Foods Market, Inc.
Category: otc | Type: HUMAN OTC DRUG LABEL
Date: 20241102

ACTIVE INGREDIENTS: ALCOHOL 62 mL/100 mL
INACTIVE INGREDIENTS: WATER; ISOPROPYL ALCOHOL; HYDROXYETHYL CELLULOSE (100 MPA.S AT 2%); CHIA SEED OIL; GLYCERIN; SUNFLOWER OIL; ROSEMARY; POLYSORBATE 20

Whole Foods 365 Lavender Hand Sanitizer Gel 32 fl oz

Active Ingredient

Ethyl Alcohol 62%

Purpose

Antiseptic

WARNINGS

For external use only. Flammable. Keep away from fire or flame.

WHEN USING

When using this productavoid contact with eyes. If eye contact occurs, rinse with water.

Stop use and ask a doctor ifskin irritation or redness develops.

Keep out of reach of children.In case of accidental ingestion, seek medical help or contact a Poison Control Center immediately.

INDICATIONS AND USAGE

Usesto help reduce bacteria on the skin

DOSAGE AND ADMINISTRATION

Directionsapply enough gel to wet hands and rub together until dry. Use 1 to 3 times daily.

STORAGE AND HANDLING

Other informationdo not store above 104°F (40°C).

Questions, Comments?

customer.questions@wholefoods.com

1-844-963-8255

INACTIVE INGREDIENT

Inactive ingredientswater, isopropyl alcohol, hydroxyethylcellulose, salvia hispanica (chia) seed oil, glycerin, helianthus annuus (sunflower) seed oil, rosmarinus officinalis (rosemary) leaf extract, fragrance (natural)*, polysorbate 20.

*Complies with ISO 9235, see www.wholefoodsmarket.com for more information.